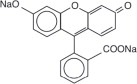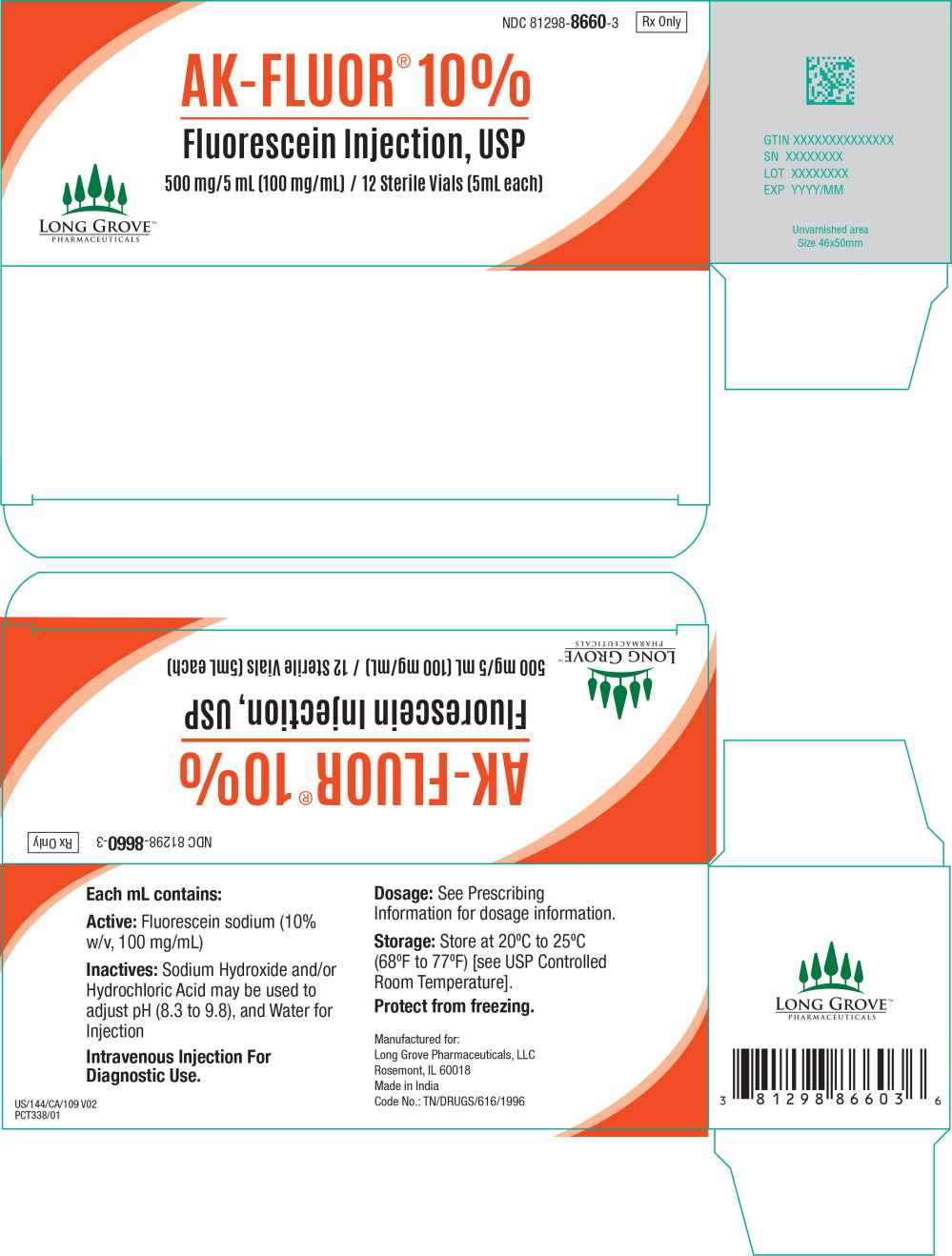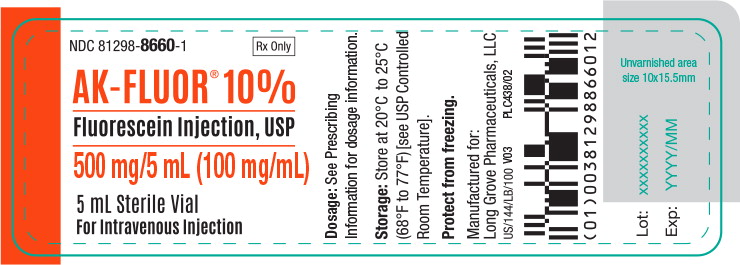 DRUG LABEL: AK-FLUOR
NDC: 81298-8660 | Form: INJECTION
Manufacturer: Long Grove Pharmaceuticals, LLC
Category: prescription | Type: HUMAN PRESCRIPTION DRUG LABEL
Date: 20241206

ACTIVE INGREDIENTS: fluorescein sodium 100 mg/1 mL
INACTIVE INGREDIENTS: sodium hydroxide; hydrochloric acid; water

HIGHLIGHTS OF PRESCRIBING INFORMATION

These highlights do not include all the information needed to use AK-FLUOR® 10% safely and effectively. See full prescribing information for AK-FLUOR® (fluorescein injection, USP) 10% Intravenous Injection.
Initial U.S. Approval: 1976

1 INDICATIONS AND USAGE

AK-FLUOR® is indicated in diagnostic fluorescein angiography or angioscopy of the retina and iris vasculature. (1)

2 DOSAGE AND ADMINISTRATION

- The normal adult dose of AK-FLUOR® 10% is 5 mL (500 mg) via intravenous administration. (2.1)
- For children, the dose should be calculated on the basis of 35 mg for each ten pounds of body weight (7.7 mg/kg body weight). (2.2)
- Do not mix or dilute with other solutions or drugs. (2.2)

3 DOSAGE FORMS AND STRENGTHS

- AK-FLUOR® (fluorescein injection, USP) 10%, 500 mg/ 5mL (100 mg/mL) is a dark reddish orange, clear solution in a 5 mL single dose vial (3)

4 CONTRAINDICATIONS

- Hypersensitivity to any component of this product. (4.1)

5 WARNINGS AND PRECAUTIONS

- Respiratory reactions (5.1)
- Severe local tissue damage (5.2)

6 ADVERSE REACTIONS

The most common adverse reactions include skin discoloration, urine discoloration, nausea, vomiting, and gastrointestinal distress

To report SUSPECTED ADVERSE REACTIONS, contact Long Grove Pharmaceuticals, LLC at 1-855-642-2594 or FDA at 1-800-FDA-1088 or www.fda.gov/medwatch. (6)

8 USE IN SPECIFIC POPULATIONS

- Caution should be exercised when fluorescein sodium is administered to a nursing woman. (8.3)

FULL PRESCRIBING INFORMATION

1 INDICATIONS AND USAGE

AK-FLUOR® 10% (100 mg/mL) is indicated in diagnostic fluorescein angiography or angioscopy of the retina and iris vasculature.

2 DOSAGE AND ADMINISTRATION

2.1 Dosing

Adult Dose

The recommended dosage of AK-FLUOR® 10% (100 mg/mL) is 500 mg via intravenous administration.

Pediatric Dose

For children, the dose is 7.7 mg/kg (actual body weight) up to a maximum of 500 mg, via intravenous infusion calculated on the basis of 35 mg for each 10 lbs. (4.54 kg) of body weight.

2.2 Preparation for Administration

Parenteral drug products should be inspected visually for particulate matter and discoloration prior to administration. Do not mix or dilute with other solutions or drugs.

2.3 Administration

Inject the dose (over 5-10 seconds is normally recommended) into the antecubital vein, after taking precautions to avoid extravasation. A syringe, filled with AK-FLUOR®, may be attached to transparent tubing and a 23 gauge butterfly needle for injection. Insert the needle and draw the patient's blood to the hub of the syringe so that a small air bubble separates the patient's blood in the tubing from the fluorescein. With the room lights on, slowly inject the blood back into the vein while watching the skin over the needle tip. If the needle has extravasated, the patient's blood will be seen to bulge the skin and the injection should be stopped before any fluorescein is injected. When assured that extravasation has not occurred, the room light may be turned off and the fluorescein injection completed. Luminescence usually appears in the retina and choroidal vessels in 7 to 14 seconds and can be observed by standard viewing equipment.

Reduction in dose from 500 mg to 200 mg of AK-FLUOR® 10% may be appropriate in cases when a highly sensitive imaging system e.g., scanning laser ophthalmoscope is used.

3 DOSAGE FORMS AND STRENGTHS

AK-FLUOR® (fluorescein injection, USP) 10%, 500 mg/ 5mL (100 mg/ml) is a dark reddish orange, clear solution in a 5 mL single-dose vial.

4 CONTRAINDICATIONS

4.1 Hypersensitivity

AK-FLUOR® is contraindicated in patients with known hypersensitivity to fluorescein sodium or any other ingredients in this product. Rare cases of death due to anaphylaxis have been reported [see Warnings and Precautions (5.1) and Adverse Reactions (6.2)].

5 WARNINGS AND PRECAUTIONS

5.1 Respiratory Reactions

Caution should be exercised in patients with a history of allergy or bronchial asthma. An emergency tray should always be available.

If a potential allergy is suspected, an intradermal skin test may be performed prior to intravenous administration, i.e., 0.05 mL injected intradermally to be evaluated 30 to 60 minutes following injection. Given the sensitivity and specificity of skin testing, a negative skin test is not proof that a patient is not allergic to fluorescein.

5.2 Severe local tissue damage

Extravasation during injection can result in severe local tissue damage due to high pH of fluorescein solution. The following complications resulting from extravasation of fluorescein have been noted to occur: Sloughing of the skin, superficial phlebitis, subcutaneous granuloma, and toxic neuritis along the median nerve in the antecubital area. Complications resulting from extravasation can cause severe pain in the arm for up to several hours. When extravasation occurs, the injection should be discontinued and conservative measures to treat damaged tissue and to relieve pain should be implemented. [see Administration (2.3) and Adverse Reactions (6.6)].

6 ADVERSE REACTIONS

6.1 Skin and urine discoloration

The most common reaction is discoloration of the skin and urine. Skin will attain a temporary yellowish discoloration. Urine attains a bright yellow color. Discoloration of the skin usually fades in 6 to 12 hours and usually fades in urine in 24 to 36 hours.

6.2 Gastrointestinal Reaction

The next most common adverse reaction is nausea. Vomiting, and gastrointestinal distress have also occurred. A strong taste may develop after injection.

6.3 Hypersensitivity Reactions

Symptoms and signs of hypersensitivity have occurred. Generalized hives and itching, bronchospasm and anaphylaxis have been reported. [see Contraindications (4.1) and Warnings and Precautions (5.1)]

6.4 Cardiopulmonary Reactions

Syncope and hypotension may occur. Cardiac arrest, basilar artery ischemia, severe shock and death may occur rarely. [see Warnings and Precautions (5.1)]

6.5 Neurologic Reactions

Headache may occur. Convulsions may rarely occur following injection.

6.6 Thrombophlebitis

Thrombophlebitis at the injection site has been reported. Extravasation of the solution at the injection site causes intense pain at the site and a dull aching pain in the injected arm. [see Administration (2.3) and Warnings and Precautions (5.2)].

8 USE IN SPECIFIC POPULATIONS

8.1 Pregnancy

Pregnancy Category C. Adequate animal reproduction studies have not been conducted with fluorescein sodium. It is also not known whether fluorescein sodium can cause fetal harm when administered to a pregnant woman. Fluorescein sodium should be given to a pregnant woman only if clearly needed.

8.3 Nursing Mothers

Fluorescein sodium has been demonstrated to be excreted in human milk. Caution should be exercised when fluorescein sodium is administered to a nursing woman.

8.4 Pediatric Use

Pediatric patients have been included in clinical studies. No overall differences in safety or effectiveness have been observed between pediatric and adult patients.

8.5 Geriatric Use

No overall differences in safety or effectiveness have been observed between elderly and other adult patients.

11 DESCRIPTION

AK-FLUOR® (fluorescein injection, USP) is a sterile solution for use intravenously as a diagnostic aid. It is a dark reddish orange solution with a pH of 8.3 to 9.8 and an osmolality of 572 to 858 mOsm/kg.

Its chemical name is spiro[isobenzofuran-1 (3H),9'-[9H]xanthene]-3-one,3'6'- dihydroxy, disodium salt.: The active ingredient is represented by the chemical structure:

MW = 376.27

AK-FLUOR® 10% contains:

Active: fluorescein sodium (10 % w/v, 100 mg/mL)

Inactives: Sodium Hydroxide and/or Hydrochloric Acid may be used to adjust pH (8.3 to 9.8), and Water for Injection.

12 CLINICAL PHARMACOLOGY

12.1 Mechanism of Action

Fluorescein sodium responds to electromagnetic radiation and light between the wavelengths of 465 to 490 nm and fluoresces, i.e., emits light at wavelengths of 520 to 530 nm. Thus, the hydrocarbon is excited by blue light and emits light that appears yellowish green. Following intravenous injection of fluorescein sodium in an aqueous solution, the unbound fraction of the fluorescein can be excited with a blue light flash from a fundus camera as it circulates through the ocular vasculature, and the yellowish green fluorescence of the dye is captured by the camera. In the fundus, the fluorescence of the dye demarcates the retinal and/or choroidal vasculature under observation, distinguishing it from adjacent areas/structures.

12.3 Pharmacokinetics

Distribution.

Within 7 to 14 seconds after IV administration into the antecubital vein, fluorescein usually appears in the central retinal artery of the eye. Within a few minutes of IV administration of fluorescein sodium, a yellowish discoloration of the skin occurs, which begins to fade 6 to 12 hours after dosing. Various estimates of volume of distribution indicate that fluorescein distributes into interstitial space (0.5 L/kg).

Metabolism.

Fluorescein is metabolized to fluorescein monoglucuronide. After IV administration of fluorescein sodium (14 mg/kg) to 7 healthy subjects, approximately 80% of fluorescein in plasma was converted to glucuronide conjugate after a period of 1 hour post dose.

Excretion.

Fluorescein and its metabolite are mainly eliminated via renal excretion. After IV administration, the urine remains slightly fluorescent for 24 to 36 hours. A renal clearance of 1.75 mL/min/kg and a hepatic clearance (due to conjugation) of 1.50 mL/min/kg have been estimated. The systemic clearance of fluorescein was essentially complete by 48 to 72 hours after administration of 500 mg fluorescein.

13 NONCLINICAL TOXICOLOGY

13.1 Carcinogenesis, Mutagenesis, Impairment of Fertility

There have been no long-term studies done using fluorescein in animals to evaluate carcinogenic potential.

16 HOW SUPPLIED/STORAGE AND HANDLING

AK-FLUOR® (fluorescein injection, USP) 10%, 500 mg/5 mL (100mg/mL) is supplied in a single-dose 5 mL glass vial with a gray chlorobutyl serum siliconized stopper and orange flip-off cap. It contains a sterile dark reddish orange solution of fluorescein sodium.

(NDC 81298-8660-3) 5 mL, single dose vials in a package of 12.

AK-FLUOR® should be stored at 20°C to 25°C (68°F to 77°F) [See USP Controlled Room Temperature]. Do not freeze. Discard unused portion.

17 PATIENT COUNSELING INFORMATION

After administration of fluorescein sodium, skin will attain a temporary yellowish discoloration. Urine attains a bright yellow color. Discoloration of the skin usually fades in 6 to 12 hours and usually fades in urine in 24 to 36 hours. [see Warnings and Precautions (6.1)].

Rx only

Manufactured for:
Long Grove Pharmaceuticals, LLC
Rosemont, IL 60018

Made in India
US/LF/077 V02 Rev. 12/24
PLF199/01

Principal Display Panel – 5 mL Carton Label

NDC 81298-8660-3

Rx Only

AK-FLU0R®10%

Fluorescein Injection, USP

500 mg/5 mL (100 mg/mL) / 12 Sterile Vials (5mL each)

LONG GROVE™
PHARMACEUTICALS

Principal Display Panel – 5 mL Vial Label

NDC 81298-8660-1

Rx Only

AK-FLU0R®10%

Fluorescein Injection, USP

500 mg/5 mL (100 mg/mL)

5 mL Sterile Vial

For Intravenous Injection